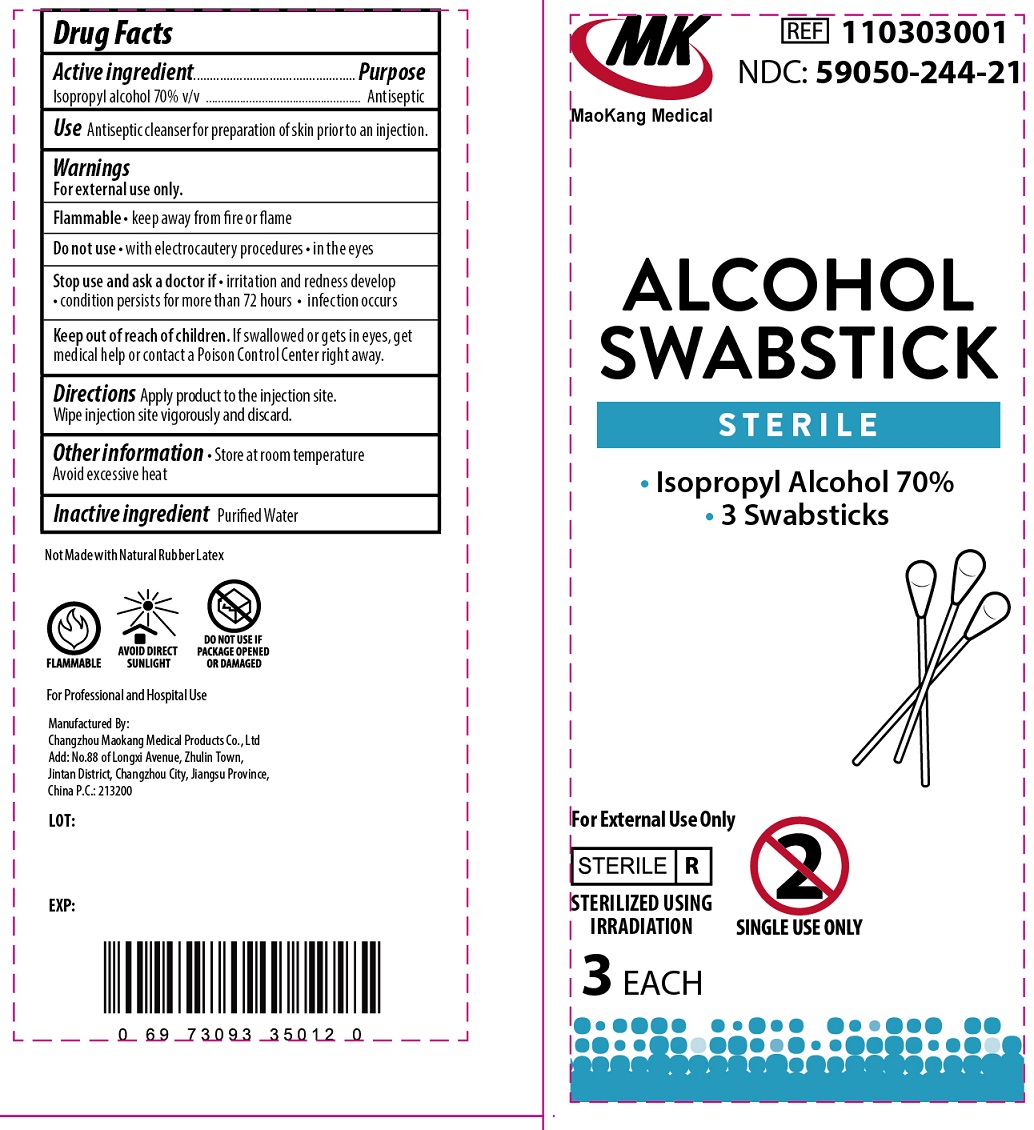 DRUG LABEL: MK Alcohol Swabstick Sterile
NDC: 59050-244 | Form: LIQUID
Manufacturer: Changzhou Maokang Medical Products Co., Ltd
Category: otc | Type: HUMAN OTC DRUG LABEL
Date: 20231109

ACTIVE INGREDIENTS: ISOPROPYL ALCOHOL 70 mL/100 mL
INACTIVE INGREDIENTS: WATER

MK Alcohol Swabstick Sterile

Active ingredient

Isopropyl Alcohol, 70% v/v

Purpose

Antiseptic

Use

Antiseptic cleanser for preparation of skin prior to injection.

Warnings

For external use only. Flammable • keep away from fire or flame

Do not use

- with electrocautery procedures
- in the eyes

Stop use and ask a doctor if

- irritation or redness develop
- condition persists for more than 72 hours
- infection occurs

Keep out of reach of children.

If swallowed or gets in eyes, get medical help or contact a Poison Control center right away.

Directions

Apply product to the injection site. Wipe injection site vigorously and discard.

Other information

Store at room temperature Avoid excessive heat

Inactive ingredients:

Purified Water